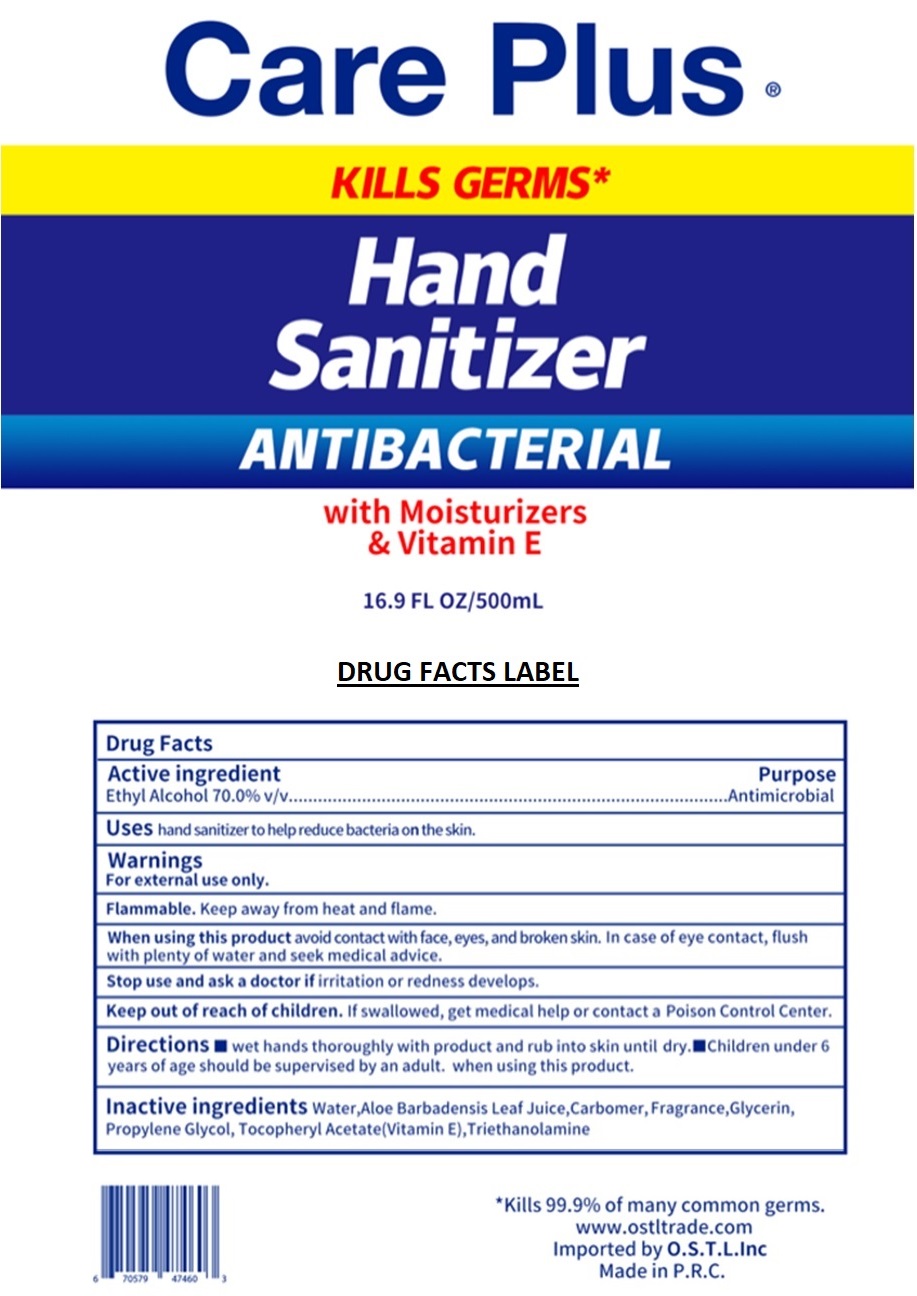 DRUG LABEL: Care Plus Hand Sanitizer
NDC: 69950-028 | Form: GEL
Manufacturer: Ostl, Inc.
Category: otc | Type: HUMAN OTC DRUG LABEL
Date: 20200622

ACTIVE INGREDIENTS: ALCOHOL 70 mL/100 mL
INACTIVE INGREDIENTS: WATER; ALOE VERA LEAF; CARBOMER HOMOPOLYMER, UNSPECIFIED TYPE; GLYCERIN; PROPYLENE GLYCOL; .ALPHA.-TOCOPHEROL ACETATE; TROLAMINE

Care Plus® Hand Sanitizer

Active ingredient

Ethyl Alcohol 70.0% v/v

Purpose

Antimicrobial

INDICATIONS AND USAGE

Uses hand sanitizer to help reduce bacteria on the skin.

Warnings

For external use only.

Flammable. Keep away from heat and flame.

When using this product avoid contact with face, eyes, and broken skin. In case of eye contact, flush with plenty of water and seek medical advice.

Stop use and ask a doctor if irritation or redness develops.

Keep out of reach of children. If swallowed, get medical help or contact a Poison Control Center.

DOSAGE AND ADMINISTRATION

Directions ▪ wet hands thoroughly with product and rub into skin until dry.▪ Children under 6 years of age should be supervised by an adult. when using this product.

INACTIVE INGREDIENT

Inactive ingredients Water, Aloe Barbadensis Leaf Juice, Carbomer,Fragrance, Glycerin, Propylene Glycol, Tocopheryl Acetate (Vitamin E), Triethanolamine

KILLS GERMS*

ANTIBACTERIAL

with Moisturizers & Vitamin E

*Kills 99.9% of many common germs.

www.ostltrade.com

Imported by O.S.T.L.Inc

Made in P.R.C.